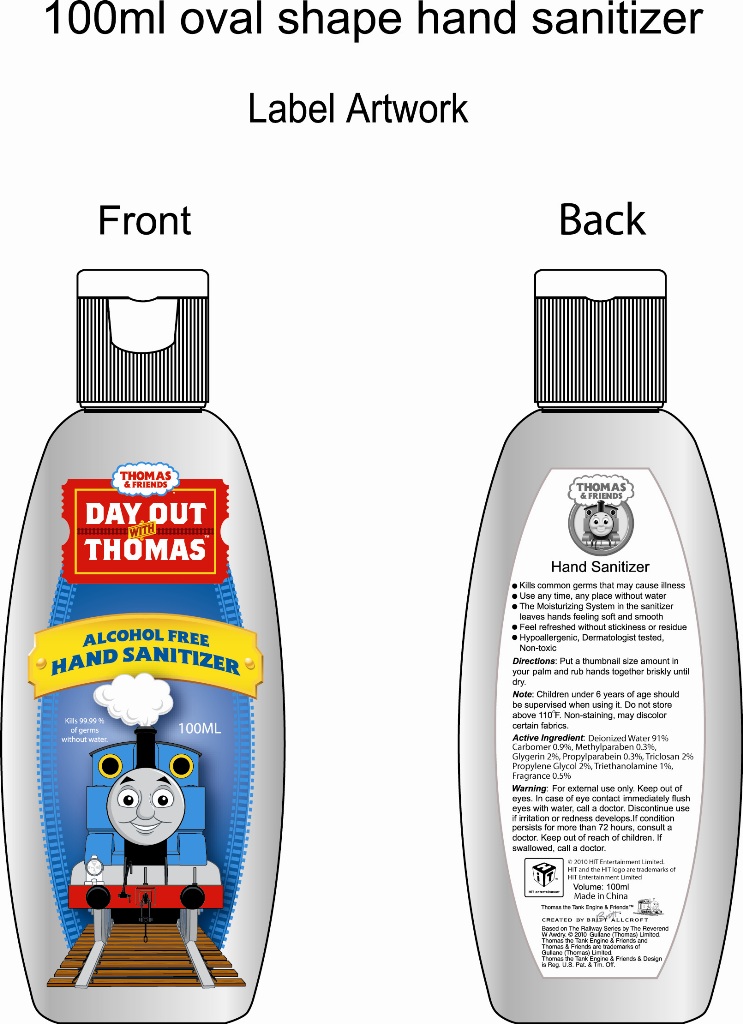 DRUG LABEL: HAND SANITIZER ALCOHOL FREE
NDC: 50260-300 | Form: GEL
Manufacturer: Fercy Personal Care Products Co Limited
Category: otc | Type: HUMAN OTC DRUG LABEL
Date: 20100406

ACTIVE INGREDIENTS: TRICLOSAN 2 mL/100 mL
INACTIVE INGREDIENTS: WATER 91.5 mL/100 mL; GLYCERIN 2 mL/100 mL; PROPYLENE GLYCOL 2 mL/100 mL; TROLAMINE 1 mL/100 mL; CARBOMER 934 0.9 mL/100 mL; Methylparaben 0.3 mL/100 mL; Propylparaben 0.3 mL/100 mL

Hand Sanitizer

Uses

Kills common germs that may cause illness
Use any time,any place without water
The moisturizing system in the sanitizer leaves hands feeling soft and smooth
Feel refreshed without stickiness or residue
Hypoallergenic,Dermatologist tested,Non-toxic

Directions

Put a thumbnail size amount in your
Palm and rub hands together briskly until dry.

Note

Children under 6 years of age should be supervised when using it. Do not store above 110℉(43 C). Non-staining, may
discolor certain fabrics.

Active Ingredient

Deionized Water 91% Carbomer 0.9%,Methylparaben 0.3%,Glygerin 2%,Propylparabein 0.3%,Triclosan 2% Propylene
Glycol 2%,Triethanolamine 1%,Fragrance 0.5%

Warning

Flammable, Keep away from fire or Flame. For external use only.
Keep out of eyes. In case of eye contact Immediately flush eyes with water, call a doctor, Discontinue use if irritation or
redness develops.
If condition persists for more than 72 hours, consult a doctor. Keep out of reach of children. If swallowed, call a doctor.

label

Enter section text here